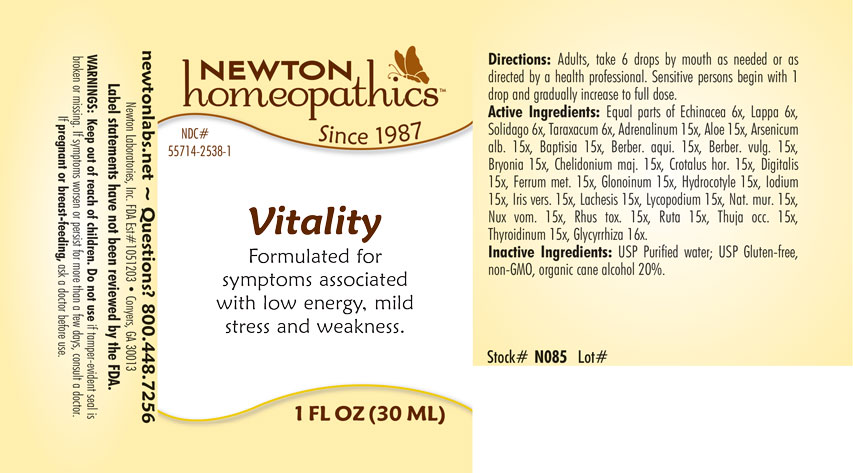 DRUG LABEL: Vitality
NDC: 55714-2538 | Form: LIQUID
Manufacturer: Newton Laboratories, Inc.
Category: homeopathic | Type: HUMAN OTC DRUG LABEL
Date: 20250210

ACTIVE INGREDIENTS: ECHINACEA, UNSPECIFIED 6 [hp_X]/1 mL; SOLIDAGO VIRGAUREA FLOWERING TOP 6 [hp_X]/1 mL; TARAXACUM OFFICINALE 6 [hp_X]/1 mL; EPINEPHRINE 15 [hp_X]/1 mL; ALOE 15 [hp_X]/1 mL; ARSENIC TRIOXIDE 15 [hp_X]/1 mL; BAPTISIA TINCTORIA ROOT 15 [hp_X]/1 mL; BERBERIS AQUIFOLIUM ROOT BARK 15 [hp_X]/1 mL; BERBERIS VULGARIS ROOT BARK 15 [hp_X]/1 mL; BRYONIA ALBA ROOT 15 [hp_X]/1 mL; CHELIDONIUM MAJUS 15 [hp_X]/1 mL; CROTALUS HORRIDUS HORRIDUS VENOM 15 [hp_X]/1 mL; DIGITALIS 15 [hp_X]/1 mL; IRON 15 [hp_X]/1 mL; NITROGLYCERIN 15 [hp_X]/1 mL; CENTELLA ASIATICA 15 [hp_X]/1 mL; IODINE 15 [hp_X]/1 mL; IRIS VERSICOLOR ROOT 15 [hp_X]/1 mL; LACHESIS MUTA VENOM 15 [hp_X]/1 mL; LYCOPODIUM CLAVATUM SPORE 15 [hp_X]/1 mL; SODIUM CHLORIDE 15 [hp_X]/1 mL; STRYCHNOS NUX-VOMICA SEED 15 [hp_X]/1 mL; TOXICODENDRON PUBESCENS LEAF 15 [hp_X]/1 mL; RUTA GRAVEOLENS FLOWERING TOP 15 [hp_X]/1 mL; THUJA OCCIDENTALIS LEAFY TWIG 15 [hp_X]/1 mL; THYROID, UNSPECIFIED 15 [hp_X]/1 mL; ARCTIUM LAPPA ROOT 6 [hp_X]/1 mL; GLYCYRRHIZA GLABRA 16 [hp_X]/1 mL
INACTIVE INGREDIENTS: ALCOHOL; WATER

Vitality 2538L

INDICATIONS & USAGE SECTION

Formulated for symptoms associated with low energy, mild stress and weakness.

DOSAGE & ADMINISTRATION SECTION

Directions: Adults, take 6 drops by mouth as needed or as directed by a health professional. Sensitive persons begin with 1 drop and gradually increase to full dose.

OTC - ACTIVE INGREDIENT SECTION

Equal parts of Echinacea 6x, Lappa major 6x, Solidago virgaurea 6x, Taraxacum officinale 6x, Adrenalinum 15x, Aloe 15x, Arsenicum album 15x, Baptisia tinctoria 15x, Berberis aquifolium 15x, Berberis vulgaris 15x, Bryonia 15x, Chelidonium majus 15x, Crotalus horridus 15x, Digitalis purpurea 15x, Ferrum metallicum 15x, Glonoinum 15x, Hydrocotyle asiatica 15x, Iodium 15x, Iris versicolor 15x, Lachesis mutus 15x, Lycopodium clavatum 15x, Natrum muriaticum 15x, Nux vomica 15x, Rhus toxicodendron 15x, Ruta graveolens 15x, Thuja occidentalis 15x, Thyroidinum 15x, Glycyrrhiza glabra 16x.

OTC - PURPOSE SECTION

Formulated for symptoms associated with low energy, mild stress and weakness.

INACTIVE INGREDIENT SECTION

Inactive Ingredients: USP Purified Water; USP Gluten-free, non-GMO, organic cane alcohol 20%

QUESTIONS SECTION

newtonlabs.net - Questions? 800.448.7256

Newton Laboratories, Inc. FDA Est # 1051203 Conyers, GA 30013

WARNINGS SECTION

WARNINGS: Keep out of reach of children. Do not use if tamper-evident seal is broken or missing. If symptoms worsen or persist for more than a few days, consult a doctor. If pregnant or breast-feeding, ask a doctor before use.

OTC - KEEP OUT OF REACH OF CHILDREN SECTION

Keep out of reach of children.